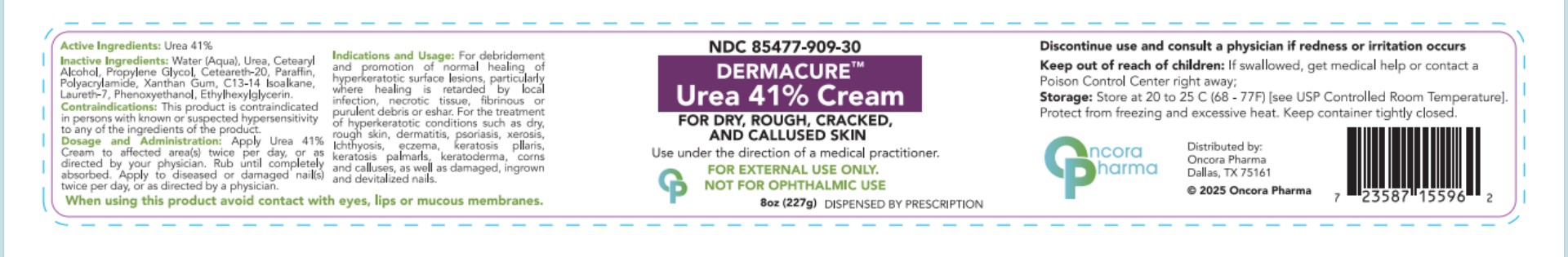 DRUG LABEL: DERMACURE
NDC: 85477-909 | Form: CREAM
Manufacturer: Oncora Pharma, LLC
Category: prescription | Type: HUMAN PRESCRIPTION DRUG LABEL
Date: 20250921

ACTIVE INGREDIENTS: UREA 410 mg/1 g
INACTIVE INGREDIENTS: CETEARETH-20; CETYL ALCOHOL; PARAFFIN; PROPYLENE GLYCOL; WATER; C13-14 ISOPARAFFIN; XANTHAN GUM; POLYACRYLAMIDE (10000 MW); ETHYLHEXYLGLYCERIN; PHENOXYETHANOL; LAURETH-7

DermaCure Urea 41% cream

INDICATIONS & USAGE

For debridement and promotion of normal healing of hyperkeratotic surface lesions, particularly where healing is retarded by local infection, necrotic tissue, ﬁbrinous or purulent debris or eshar. Urea is useful for the treatment of hyperkeratotic conditions such as dry, rough skin, dermatitis, psoriasis, xerosis, ichthyosis, eczema, keratosis pilaris, keratosis palmaris, keratoderma, corns and calluses, as well as damaged, ingrown and devitalized nails.

CONTRAINDICATIONS

This product is contraindicated in persons with known or suspected hypersensitivity to any of the ingredients of the product.

WARNINGS

Avoid contact with eyes, lips and mucous membranes.

ADVERSE REACTIONS:

Discontinue use and consult a physician if redness or irritation occurs.

DOSAGE AND ADMINISTRATION

Apply Urea 41% to affected skin twice per day, or as directed by your physician. Rub in until completely absorbed.

Apply to diseased or damaged nail(s) twice per day, or as directed by a physician.

HOW SUPPLIED

DERMACURE Urea 41% Cream 8 oz. (227 g): NDC 85477-909-30

STORAGE

Store at 20° to 25°C (68° to 77°F) [see USP Controlled
Room Temperature]. Protect from freezing and excessive
heat. Keep container tightly closed.

KEEP THIS AND ALL MEDICATIONS OUT OF THE REACH OF CHILDREN.

DERMACURE™

Distributed by

Oncora Pharma

Dallas, TX 75161